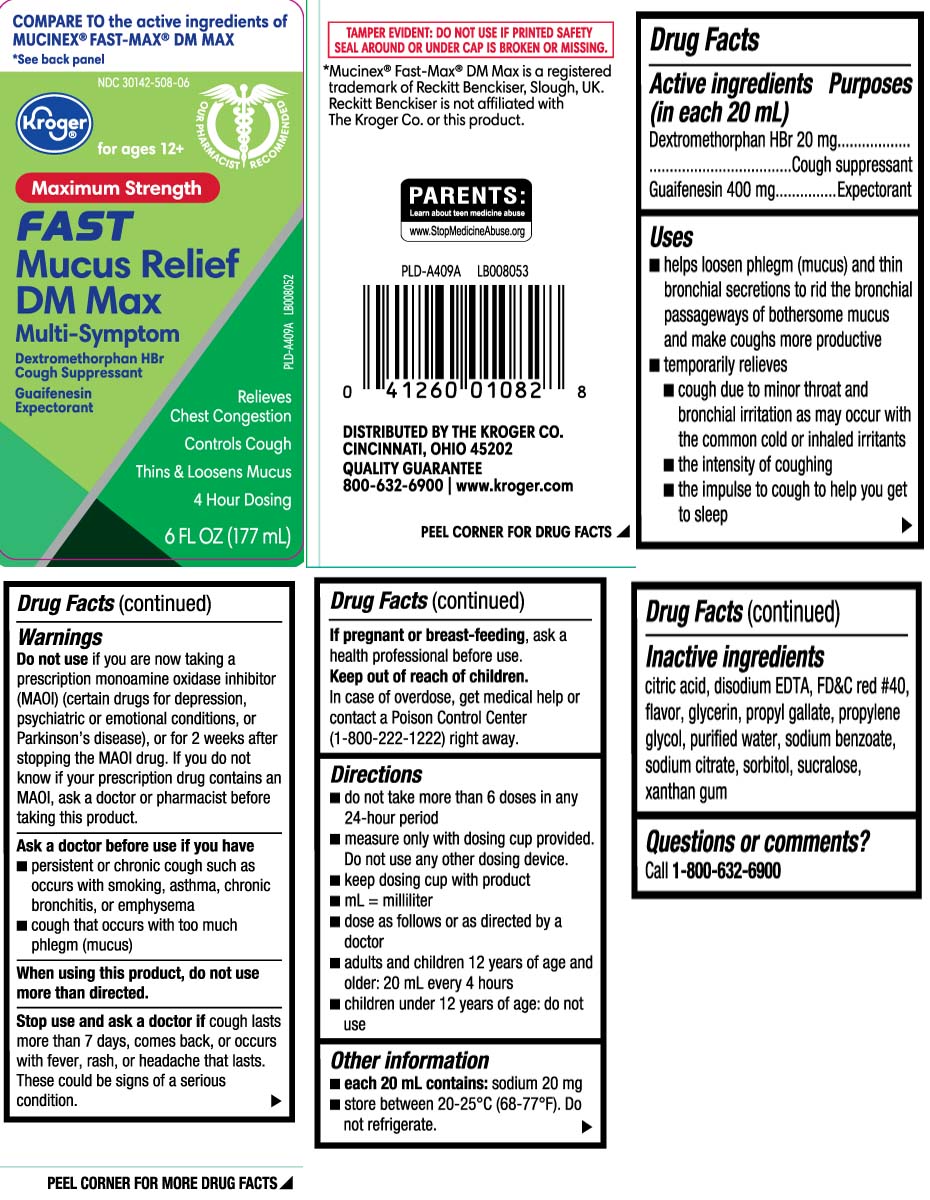 DRUG LABEL: Mucus Relief DM
NDC: 30142-508 | Form: LIQUID
Manufacturer: The Kroger Co.
Category: otc | Type: HUMAN OTC DRUG LABEL
Date: 20240610

ACTIVE INGREDIENTS: DEXTROMETHORPHAN HYDROBROMIDE 20 mg/20 mL; GUAIFENESIN 400 mg/20 mL
INACTIVE INGREDIENTS: ANHYDROUS CITRIC ACID; EDETATE DISODIUM; FD&C RED NO. 40; GLYCERIN; PROPYL GALLATE; PROPYLENE GLYCOL; WATER; SODIUM BENZOATE; TRISODIUM CITRATE DIHYDRATE; SORBITOL; SUCRALOSE; XANTHAN GUM

Drug Facts

Active ingredients (in each 20 mL)

Dextromethorphan HBr 20 mg

Guaifenesin 400 mg

Purpose

Cough suppressant

Expectorant

Uses

- helps loosen phlegm (mucus) and thin bronchial secretions to make coughs more productive
- temporarily relieves
  - cough due to minor throat and bronchial irritation as may occur with the common cold or inhaled irritants
  - the intensity of coughing
  - the impulse to cough to help you get to sleep

Warnings

Do not use

if you are now taking a prescription monoamine oxidase inhibitor (MAOI) (certain drugs for depression, psychiatric or emotional conditions, or Parkinson’s disease), or for 2 weeks after stopping the MAOI drug. If you do not know if your prescription drug contains an MAOI, ask a doctor or pharmacist before taking this product.

Ask a doctor before use if you have

- persistent or chronic cough such as occurs with smoking, asthma, chronic bronchitis, or emphysema
- cough accompanied by too much phlegm (mucus)

When using this product,

do not use more than directed.

Stop use and ask a doctor if

cough lasts more than 7 days, comes back, or occurs with fever, rash or persistent headache. These could be signs of a serious condition.

If pregnant or breast-feeding,

ask a health professional before use.

Keep out of reach of children.

In case of overdose, get medical help or contact a Poison Control Center (1-800-222-1222) right away.

Directions

- do not take more than 6 doses in any 24-hour period
- measure only with dosing cup provided. Do not use any other device
- keep dosing cup with product
- mL = milliliter
- dose as follows or as directed by a doctor
- adults and children 12 years of age and older: 20 mL every 4 hours
- children under 12 years of age: do not use

Other information

- each 20 mL contains: sodium 20 mg
- store between 20-25°C (68-77°F). Do not refrigerate.

Inactive ingredients

citric acid, disodium EDTA, FD&C red #40, flavor, glycerin, propyl gallate, propylene glycol, purified water, sodium benzoate, sodium citrate, sorbitol, sucralose, xanthan gum

Questions or comments?

Call 1-800-632-6900

Principal Display Panel

COMPARE TO the active ingredients of MUCINEX® FAST-MAX® DM MAX

for ages 12+

maximum Strength

FAST

Mucus Relief

DM Max

multi-Symptom

Dextromethorphan HBr 20 mg

Cough Suppressant

Guaifenesin 400 mg

Expectorant

Relieves

Chest Congestion

Controls Cough

Thin & Loosens Mucus

4 Hour Dosing

*Mucinex® Fast-Max® DM Max is a registered trademark of Reckitt Benckiser, Slough, UK. Reckitt Benckiser is not affiliated with The Kroger Co. or this product

TAMPER EVIDENT: DO NOT USE IF PRINTED SAFETY SEAL UNDER CAP IS BROKEN OR MISSING.

DISTRIBUTED BY: THE KROGER CO.

CINCINNATI, OHIO 45202

www.kroger.com

Package Label

KROGER Maximum Strength Mucus Relief DM